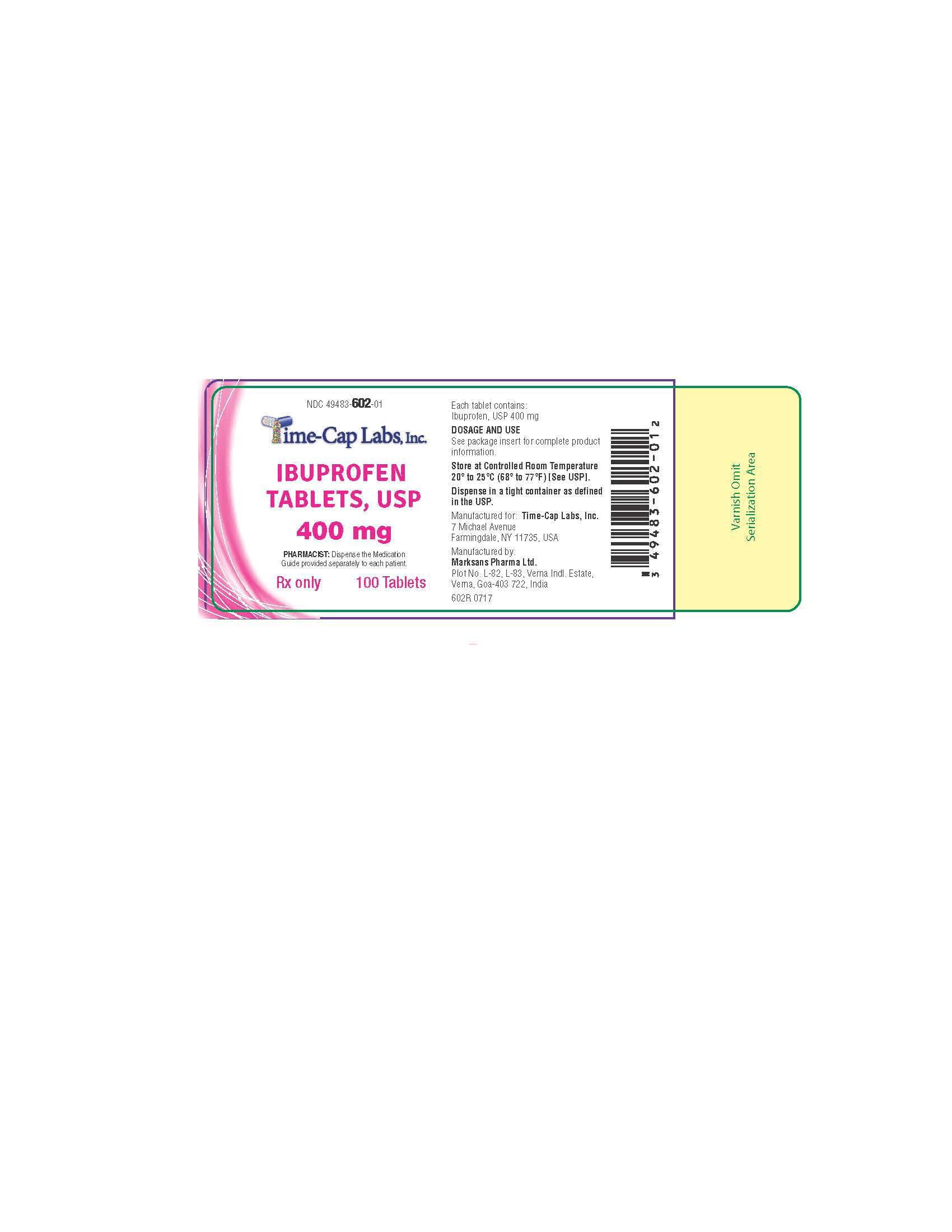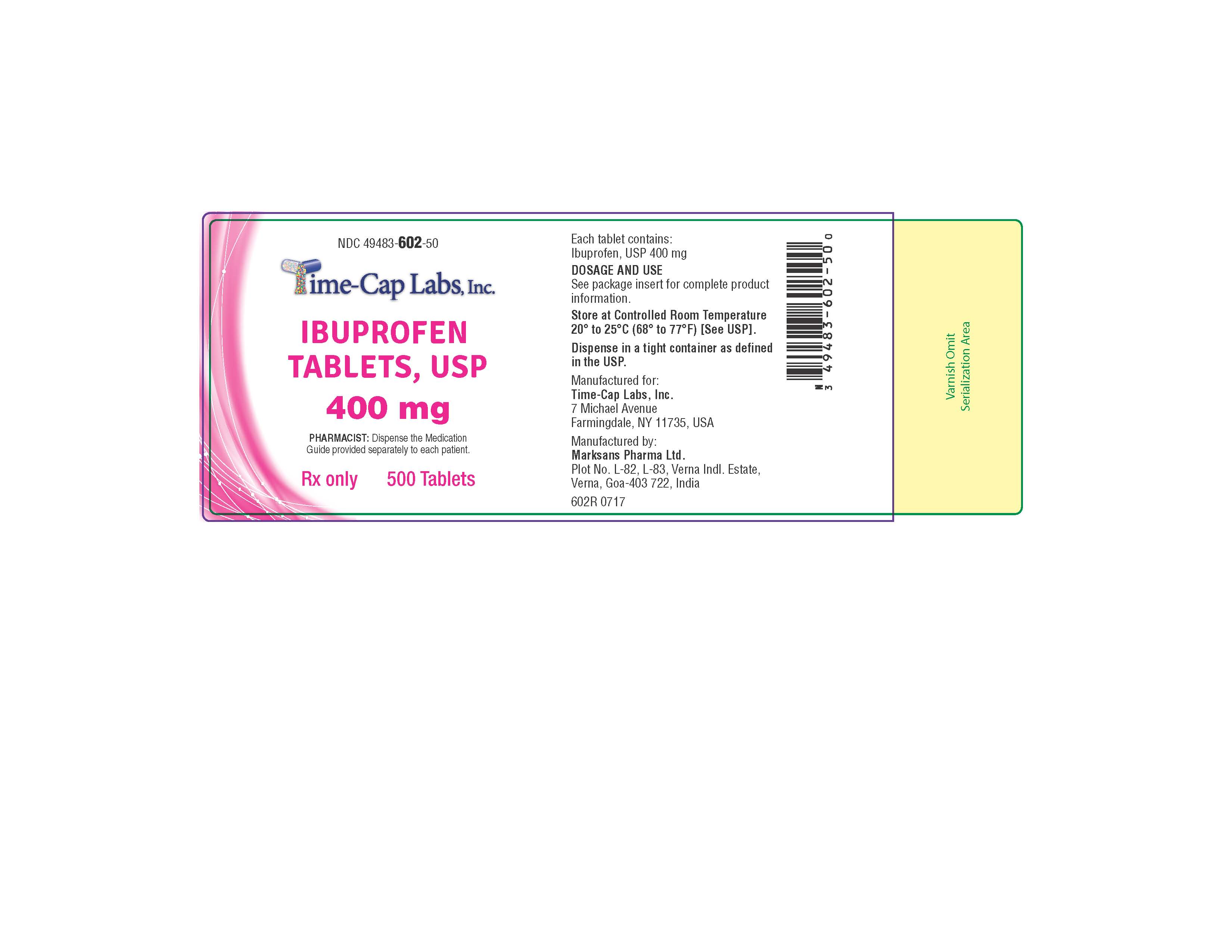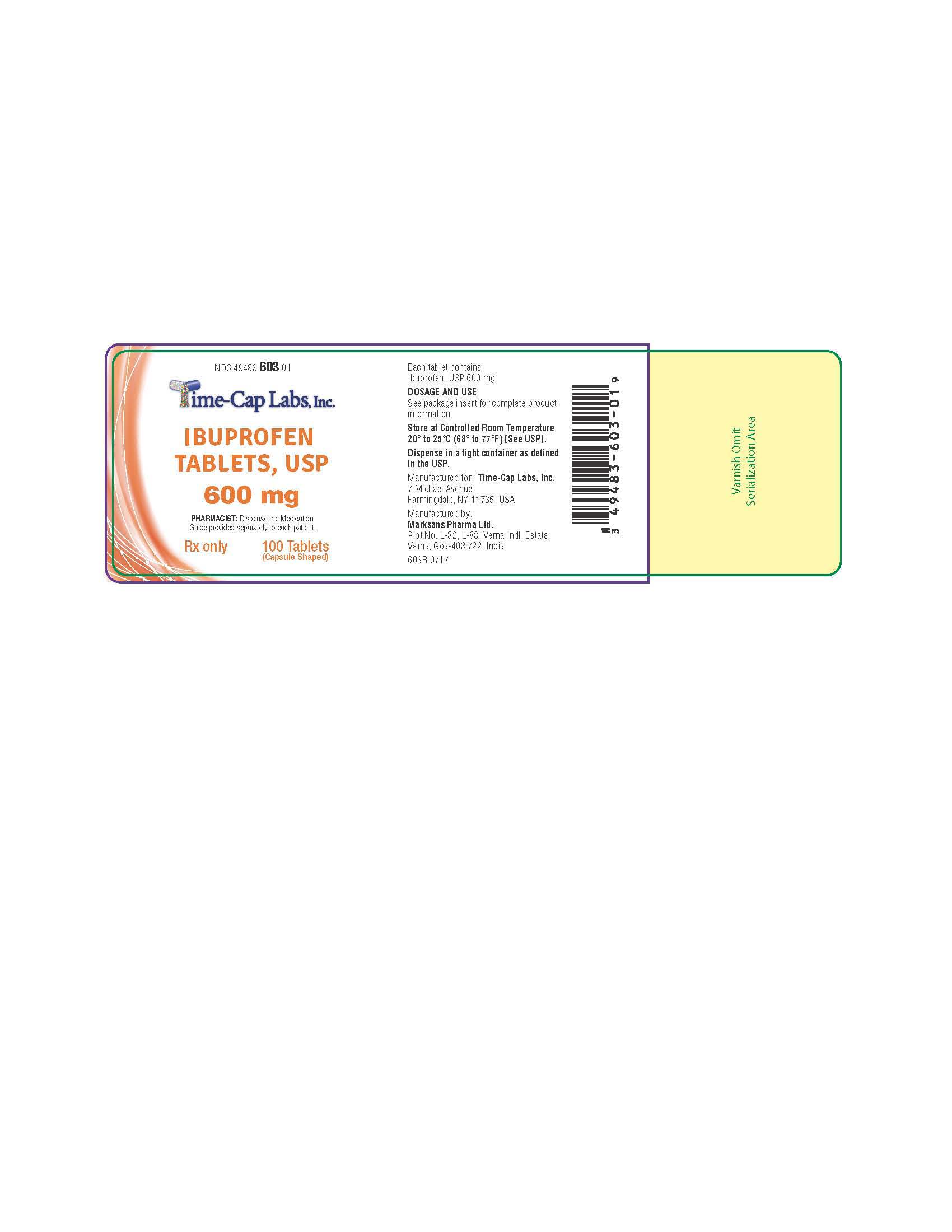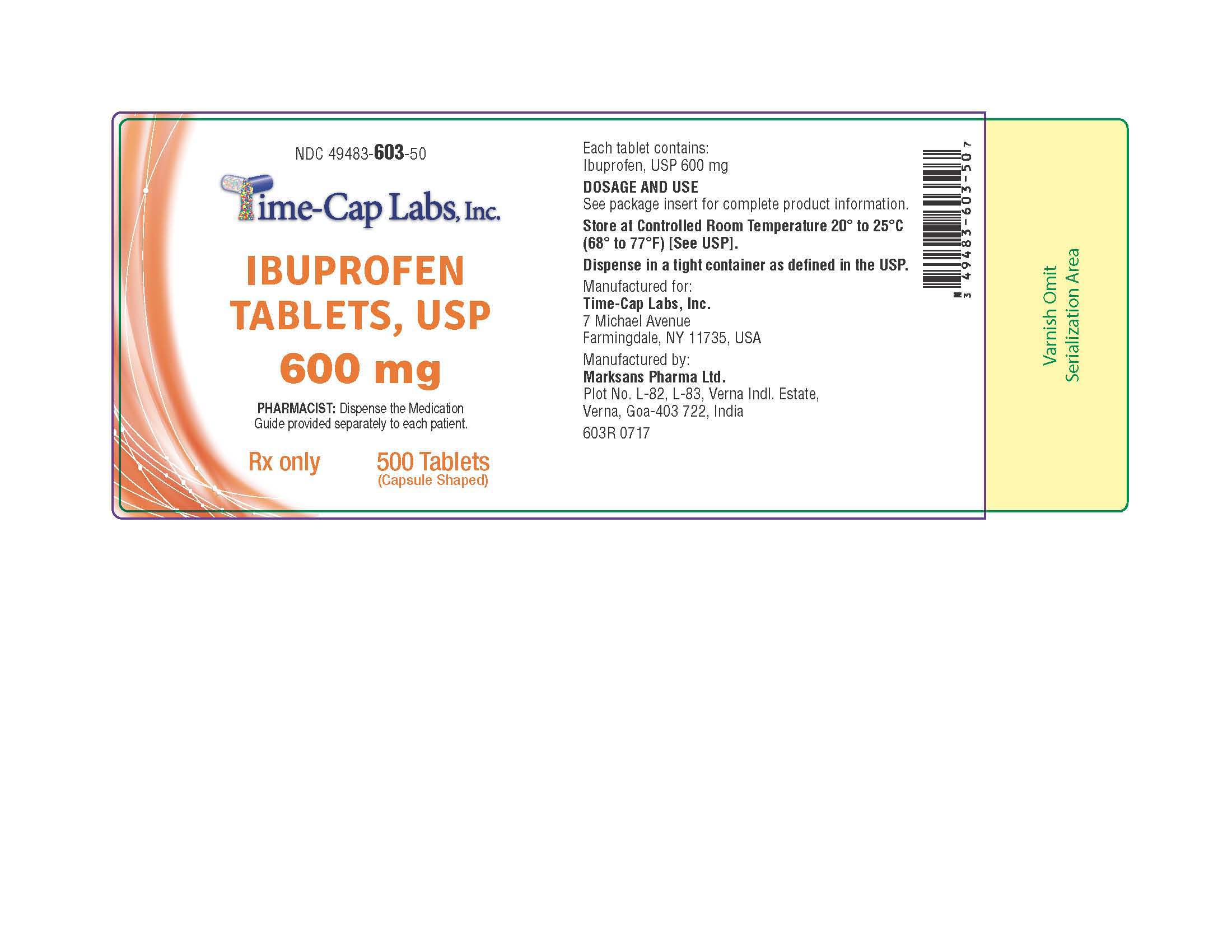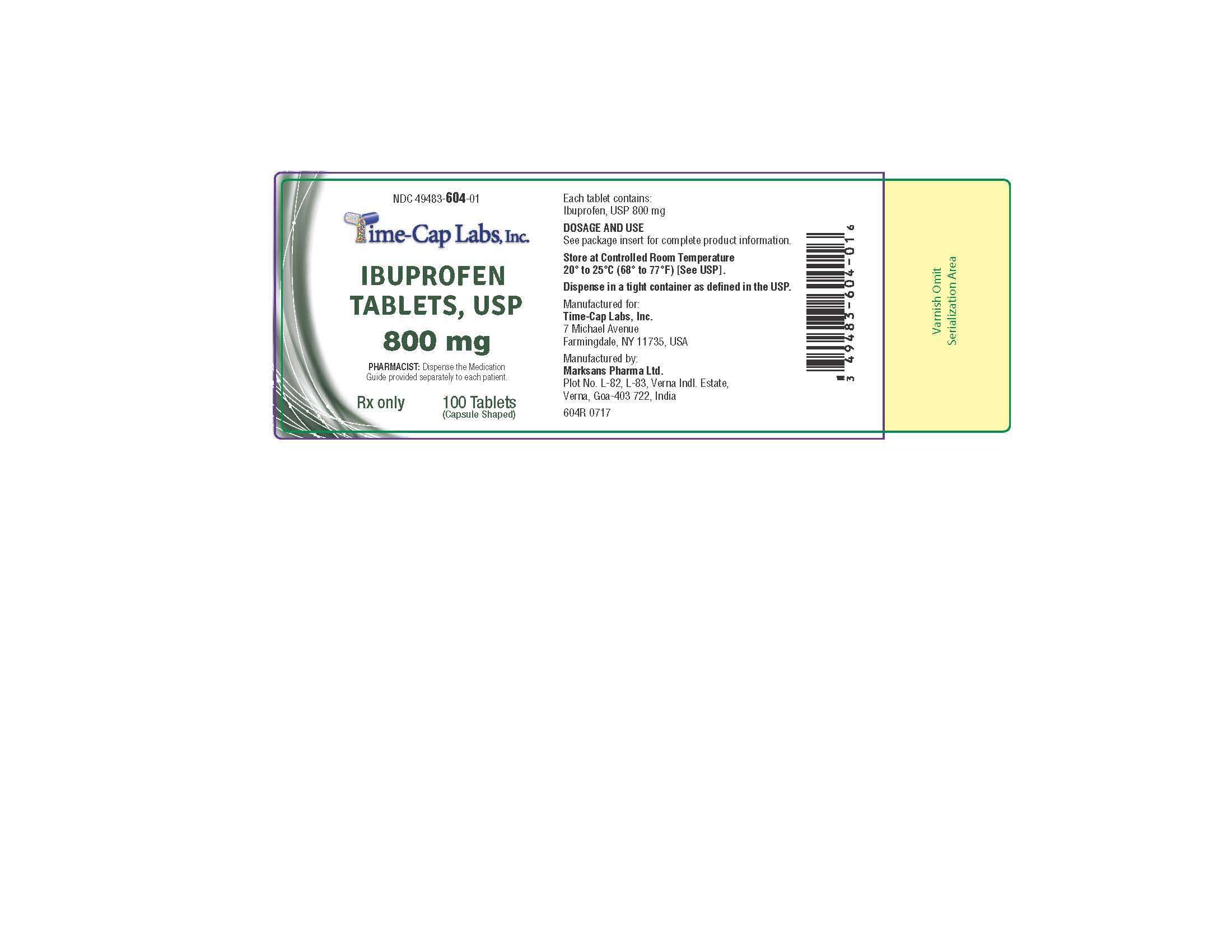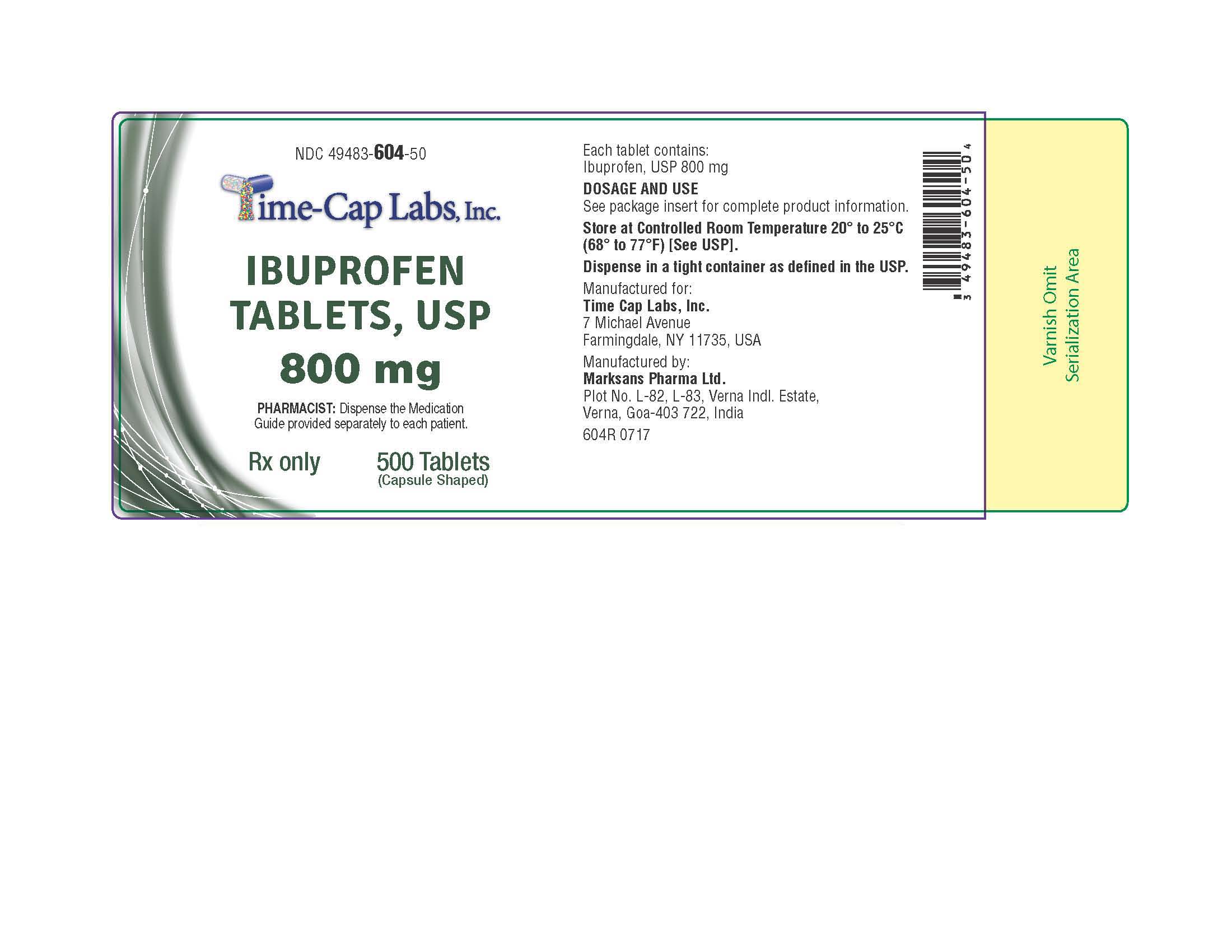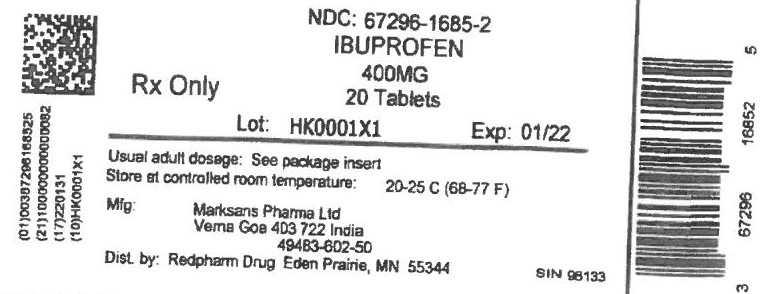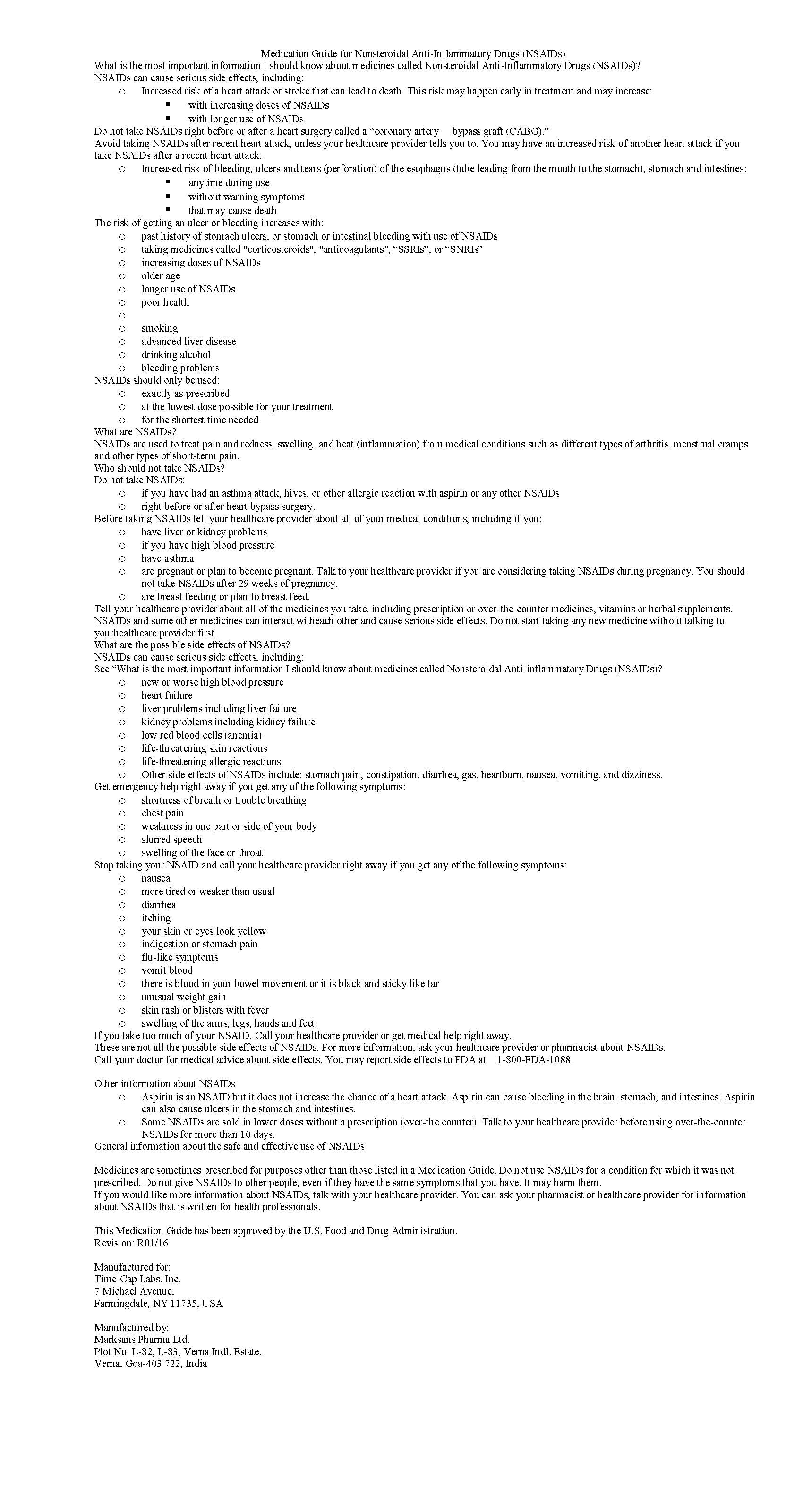 DRUG LABEL: IBUPROFEN
NDC: 67296-1685 | Form: TABLET, FILM COATED
Manufacturer: RedPharm Drug, Inc.
Category: prescription | Type: HUMAN PRESCRIPTION DRUG LABEL
Date: 20240803

ACTIVE INGREDIENTS: IBUPROFEN 400 mg/1 1
INACTIVE INGREDIENTS: SILICON DIOXIDE; CROSCARMELLOSE SODIUM; MAGNESIUM STEARATE; CELLULOSE, MICROCRYSTALLINE; POLYETHYLENE GLYCOL, UNSPECIFIED; POLYVINYL ALCOHOL; STARCH, PREGELATINIZED CORN; TALC; TITANIUM DIOXIDE

IBUPROFEN 400 MG tablets

HOW SUPPLIED

400mg (white to of white, round, biconvex, film coated tablets debossed with '121' on one side and plain on the other side) Bottles of 100 & 500

HOW SUPPLIED

600mg (white to off white, capsule shaped, biconvex, film coated tablets debossed with '122' on one side and plain on the other side) Bottles of 30, 50, 100 & 500

HOW SUPPLIED

800 mg (white to off-white, capsule shaped, biconvex, film-coated tablets debossed with ‘123’ on one side and plain on other side)